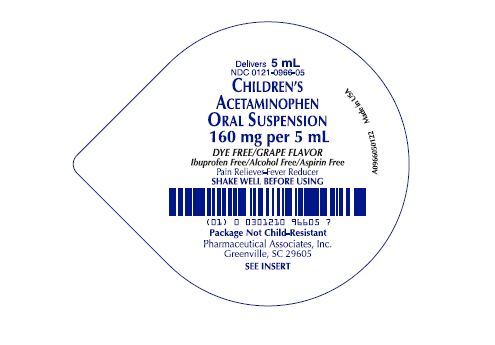 DRUG LABEL: Dye Free Childrens Acetaminophen
NDC: 0121-0966 | Form: SUSPENSION
Manufacturer: PAI Holdings, LLC dba PAI Pharma
Category: otc | Type: HUMAN OTC DRUG LABEL
Date: 20250204

ACTIVE INGREDIENTS: ACETAMINOPHEN 160 mg/5 mL
INACTIVE INGREDIENTS: MAGNESIUM ALUMINUM SILICATE; ACESULFAME POTASSIUM; BUTYLPARABEN; ANHYDROUS CITRIC ACID; HIGH FRUCTOSE CORN SYRUP; POLYSORBATE 80; PROPYLENE GLYCOL; WATER; SODIUM BENZOATE; SORBITOL SOLUTION; XANTHAN GUM

Dye Free Childrens Acetaminophen
Drug Facts

Active ingredient

(in each 5 mL)
Acetaminophen 160 mg

Purpose

Acetaminophen
160 mg.............................Pain reliever/fever reducer

Uses temporarily:

- reduces fever
- minor aches and pains due to:

• the common cold • flu • headache • sore throat • toothache

Warnings

Liver warning: This product contains acetaminophen. Severe liver damage may occur if your child takes:
• more than 5 doses in 24 hours, which is the maximum daily amount
• with other drugs containing acetaminophen

Allergy alert: acetaminophen may cause severe skin reactions.
Symptoms may include:
• skin reddening
• blisters
• rash
If a skin reaction occurs, stop use and seek medical help right away.

Sore throat warning: If sore throat is severe, persists for more than 2 days, is accompanied or followed by fever, headache, rash, nausea, or vomiting, consult a doctor promptly.

Do not use

- with any other drug containing acetaminophen (prescription or non-prescription). If you are not sure whether a drug contains
  acetaminophen, ask a doctor or pharmacist.
- if your child is allergic to acetaminophen or any of the inactive ingredients in this product

Ask a doctor before use if your child has liver disease.

Ask a doctor or pharmacist before use if your child is taking the blood thinning drug warfarin

When using this product do not exceed recommended dose (see overdose warning)

Stop use and ask a doctor if:

• pain gets worse or lasts more than 5 days
• fever gets worse or lasts more than 3 days
• new symptoms occur
• redness or swelling is present

These could be signs of a serious condition.

Keep out of reach of children.

Overdose Warning:

In case of overdose, get medical help or contact a Poison Control Center right away. (1-800-222-1222). Quick medical attention is critical for adults as well as children even if you do not notice any sign or symptoms.

Directions

- this product does not contain directions or complete warnings for adult use.
- do not take more than directed (see overdose warning)
- shake well before using
- mL = milliliter
- find right dose on chart below. If possible, use weight to dose; otherwise, use age
- repeat dose every 4 hours while symptoms last
- do not give more than 5 times in 24 hours

Attention: For Single-Dose Cups, the entire dose should be taken.

Weight (lb) Age (yr) Dose (mL)*
under 24 under 2 years ask a doctor
24-35 2-3 years 5 mL
36-47 4-5 years 7.5 mL
48-59 6-8 years 10 mL
60-71 9-10 years 12.5 mL
72-95 11 years 15 mL

*or as directed by a doctor

Other information

- each 5 mL contains: sodium: 2 mg
- Store at 20° to 25°C (68° to 77°F)
- grape flavored suspension supplied in the following oral dosage form:

NDC 0121-0966-05: 5 mL unit dose cup, in a tray of ten cups.

NDC 0121-0966-94: Case contains 30 unit dose cups of 5 mL (0121-0966-05) packaged in 3 trays of 10 unit dose cups each.
NDC 0121-0966-00: Case contains 100 unit dose cups of 5 mL (0121-0966-05) packaged in 10 trays of 10 unit dose cups each.

INACTIVE INGREDIENT

Inactive ingredients: acesulfame K, butylparaben, citric acid, flavoring, glycerin, high fructose corn syrup, polysorbate 80, propylene glycol, purified water, sodium benzoate, sorbitol solution, veegum and xanthan gum.

Questions or Comments?

Call 1-800-845-8210.

MANUFACTURED BY:

Pharmaceutical Associates, Inc.

Greenville, SC 29605

www.paipharma.com

R01/22

Principal Display Panel

Delivers 5 mL

NDC 0121-0966-05

DYE FREE/GRAPE FLAVOR

Children's Acetaminophen Oral Suspension

160 mg per 5 mL

DYE FREE/GRAPE FLAVOR

Ibuprofen Free/Alcohol Free/Aspirin Free

Pain Reliever-Fever Reducer

SHAKE WELL BEFORE USING

Package Not Child-Resistant

Pharmaceutical Associates, Inc.

SEE INSERT